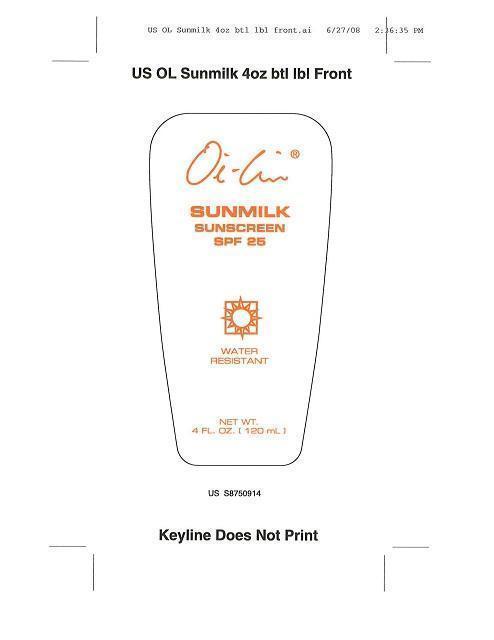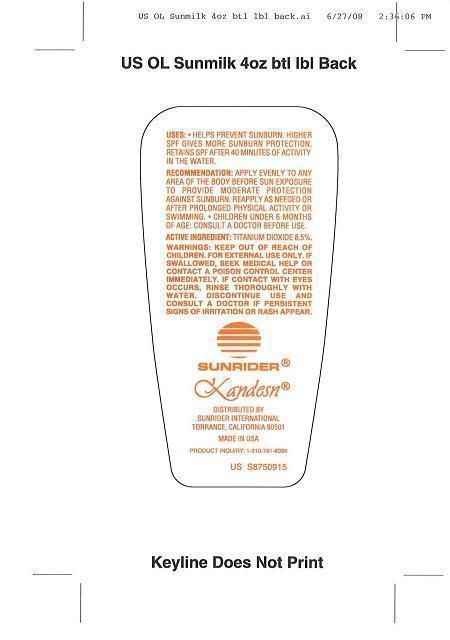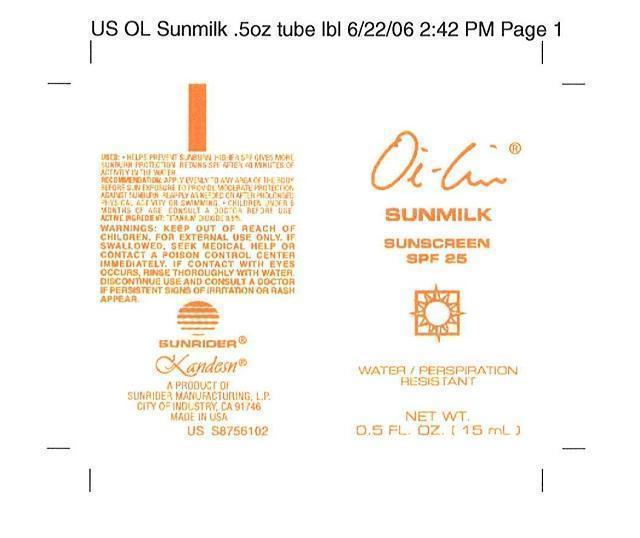 DRUG LABEL: OI LIN SUNMILK SUNSCREEN SPF 25
NDC: 62191-012 | Form: EMULSION
Manufacturer: Sunrider Manufacturing L.P.
Category: otc | Type: HUMAN OTC DRUG LABEL
Date: 20130213

ACTIVE INGREDIENTS: TITANIUM DIOXIDE 85 mg/1 g
INACTIVE INGREDIENTS: 2-HYDROXYETHYL ACRYLATE; ALANINE; ALOE VERA LEAF; ALUMINUM HYDROXIDE; ARGININE; BETAINE; BUTYLENE GLYCOL; CETYL PEG/PPG-10/1 DIMETHICONE (HLB 1.5); CYCLOMETHICONE 5; DIMETHICONE; EDETATE DISODIUM; GLUTAMIC ACID; GLYCINE; HEXYL LAURATE; HYALURONATE SODIUM; isononyl isononanoate; LYSINE; OAT; PHENOXYETHANOL; POLYGLYCERYL-4 ISOSTEARATE; POLYSORBATE 60; PROLINE; SERINE; SODIUM CHLORIDE; SODIUM HYDROXYMETHYLGLYCINATE    ; SODIUM MYRISTOYL SARCOSINATE; SODIUM PYRROLIDONE CARBOXYLATE; SORBITOL; SQUALANE; THREONINE; WATER

OIL LIN® SUNMILK SUNSCREEN SPF 25

ACTIVE INGREDIENT: TITANIUM DIOXIDE 8.5%

INACTIVE INGREDIENT: WATER (DEIONIZED)

PURPOSE

USES: HELPS PREVENT SUNBURN.

INDICATIONS AND USAGE

RECOMMENDATION: APPPLY EVENLY TO ANY AREA OF THE BODY BEFORE SUN EXPOSURE TO PROVIDE MODERATE PROTECTION AGAINST SUNBURN. REAPPLY AS NEEDED OR AFTER PROLONGED PHYSICAL ACTIVITY OR SWIMMING. HIGHER SPF GIVES MORE SUNBURN PROTECTION. RETAINS SPF AFTER 40 MINUTES OF ACTIVITY IN THE WATER. CHILDREN UNDER 6 MONTHS OF AGE:CONSULT A DOCTOR BEFORE USE.

WARNINGS

WARNING: FOR EXTERNAL USE ONLY, IF SWALLOWED SEEK MEDICAL HELP OR CONTACT A POISON CONTROL CENTER IMMEDIATELY, IF CONTACT WITH EYES OCCURS, RINSE THOROUGHLY WITH WATER, DISCONTINUE USE AND CONSULT A DOCTOR IF PERSISTENT SIGNS OF IRRITATION OR RASH APPEAR

KEEP OUT OF REACH OF CHILDREN.

PACKAGE LABEL

MM1MM2MM3